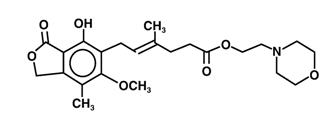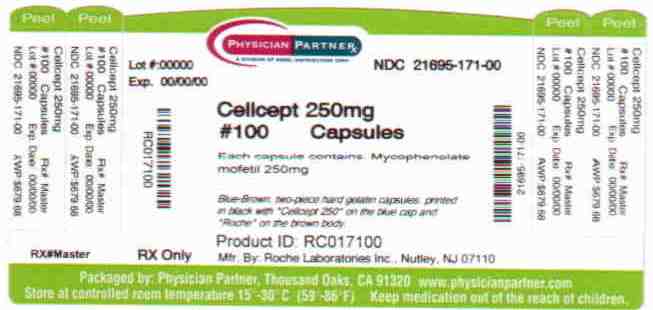 DRUG LABEL: CellCept
NDC: 21695-171 | Form: CAPSULE
Manufacturer: Rebel Distributors Corp
Category: prescription | Type: HUMAN PRESCRIPTION DRUG LABEL
Date: 20110513

ACTIVE INGREDIENTS: Mycophenolate Mofetil 250 mg/1 1
INACTIVE INGREDIENTS: croscarmellose sodium; magnesium stearate; Povidone K90; starch, corn; ferrosoferric oxide; FD&C blue No. 2; gelatin; ferric oxide yellow; ferric oxide red; titanium dioxide; silicon dioxide; sodium lauryl sulfate

CellCept®
(mycophenolate mofetil capsules)

BOXED WARNING

Immunosuppression may lead to increased susceptibility to infection and possible development of lymphoma. Only physicians experienced in immunosuppressive therapy and management of renal, cardiac or hepatic transplant patients should use CellCept. Patients receiving the drug should be managed in facilities equipped and staffed with adequate laboratory and supportive medical resources. The physician responsible for maintenance therapy should have complete information requisite for the follow-up of the patient.

Female users of childbearing potential must use contraception. Use of CellCept during pregnancy is associated with increased risk of pregnancy loss and congenital malformations.

DESCRIPTION

CellCept (mycophenolate mofetil) is the 2-morpholinoethyl ester of mycophenolic acid (MPA), an immunosuppressive agent; inosine monophosphate dehydrogenase (IMPDH) inhibitor.

The chemical name for mycophenolate mofetil (MMF) is 2-morpholinoethyl (E)-6-(1,3-dihydro-4-hydroxy-6-methoxy-7-methyl-3-oxo-5-isobenzofuranyl)-4-methyl-4-hexenoate. It has an empirical formula of C23H31NO7, a molecular weight of 433.50, and the following structural formula:

Mycophenolate mofetil is a white to off-white crystalline powder. It is slightly soluble in water (43 µg/mL at pH 7.4); the solubility increases in acidic medium (4.27 mg/mL at pH 3.6). It is freely soluble in acetone, soluble in methanol, and sparingly soluble in ethanol. The apparent partition coefficient in 1-octanol/water (pH 7.4) buffer solution is 238. The pKa values for mycophenolate mofetil are 5.6 for the morpholino group and 8.5 for the phenolic group.

Mycophenolate mofetil hydrochloride has a solubility of 65.8 mg/mL in 5% Dextrose Injection USP (D5W). The pH of the reconstituted solution is 2.4 to 4.1.

CellCept is available for oral administration as capsules containing 250 mg of mycophenolate mofetil, tablets containing 500 mg of mycophenolate mofetil, and as a powder for oral suspension, which when constituted contains 200 mg/mL mycophenolate mofetil.

Inactive ingredients in CellCept 250 mg capsules include croscarmellose sodium, magnesium stearate, povidone (K-90) and pregelatinized starch. The capsule shells contain black iron oxide, FD&C blue #2, gelatin, red iron oxide, silicon dioxide, sodium lauryl sulfate, titanium dioxide, and yellow iron oxide.

Inactive ingredients in CellCept 500 mg tablets include black iron oxide, croscarmellose sodium, FD&C blue #2 aluminum lake, hydroxypropyl cellulose, hydroxypropyl methylcellulose, magnesium stearate, microcrystalline cellulose, polyethylene glycol 400, povidone (K-90), red iron oxide, talc, and titanium dioxide; may also contain ammonium hydroxide, ethyl alcohol, methyl alcohol, n-butyl alcohol, propylene glycol, and shellac.

Inactive ingredients in CellCept Oral Suspension include aspartame, citric acid anhydrous, colloidal silicon dioxide, methylparaben, mixed fruit flavor, sodium citrate dihydrate, sorbitol, soybean lecithin, and xanthan gum.

CellCept Intravenous is the hydrochloride salt of mycophenolate mofetil. The chemical name for the hydrochloride salt of mycophenolate mofetil is 2-morpholinoethyl (E)-6-(1,3-dihydro-4-hydroxy-6-methoxy-7-methyl-3-oxo-5-isobenzofuranyl)-4-methyl-4-hexenoate hydrochloride. It has an empirical formula of C23H31NO7 HCl and a molecular weight of 469.96.

CellCept Intravenous is available as a sterile white to off-white lyophilized powder in vials containing mycophenolate mofetil hydrochloride for administration by intravenous infusion only. Each vial of CellCept Intravenous contains the equivalent of 500 mg mycophenolate mofetil as the hydrochloride salt. The inactive ingredients are polysorbate 80, 25 mg, and citric acid, 5 mg. Sodium hydroxide may have been used in the manufacture of CellCept Intravenous to adjust the pH. Reconstitution and dilution with 5% Dextrose Injection USP yields a slightly yellow solution of mycophenolate mofetil, 6 mg/mL. (For detailed method of preparation, see DOSAGE AND ADMINISTRATION).

CLINICAL PHARMACOLOGY

Mechanism of Action

Mycophenolate mofetil has been demonstrated in experimental animal models to prolong the survival of allogeneic transplants (kidney, heart, liver, intestine, limb, small bowel, pancreatic islets, and bone marrow).

Mycophenolate mofetil has also been shown to reverse ongoing acute rejection in the canine renal and rat cardiac allograft models. Mycophenolate mofetil also inhibited proliferative arteriopathy in experimental models of aortic and cardiac allografts in rats, as well as in primate cardiac xenografts. Mycophenolate mofetil was used alone or in combination with other immunosuppressive agents in these studies. Mycophenolate mofetil has been demonstrated to inhibit immunologically mediated inflammatory responses in animal models and to inhibit tumor development and prolong survival in murine tumor transplant models.

Mycophenolate mofetil is rapidly absorbed following oral administration and hydrolyzed to form MPA, which is the active metabolite. MPA is a potent, selective, uncompetitive, and reversible inhibitor of inosine monophosphate dehydrogenase (IMPDH), and therefore inhibits the de novo pathway of guanosine nucleotide synthesis without incorporation into DNA. Because T- and B-lymphocytes are critically dependent for their proliferation on de novo synthesis of purines, whereas other cell types can utilize salvage pathways, MPA has potent cytostatic effects on lymphocytes. MPA inhibits proliferative responses of T- and B-lymphocytes to both mitogenic and allospecific stimulation. Addition of guanosine or deoxyguanosine reverses the cytostatic effects of MPA on lymphocytes. MPA also suppresses antibody formation by B-lymphocytes. MPA prevents the glycosylation of lymphocyte and monocyte glycoproteins that are involved in intercellular adhesion to endothelial cells and may inhibit recruitment of leukocytes into sites of inflammation and graft rejection. Mycophenolate mofetil did not inhibit early events in the activation of human peripheral blood mononuclear cells, such as the production of interleukin-1 (IL-1) and interleukin-2 (IL-2), but did block the coupling of these events to DNA synthesis and proliferation.

Pharmacokinetics

Following oral and intravenous administration, mycophenolate mofetil undergoes rapid and complete metabolism to MPA, the active metabolite. Oral absorption of the drug is rapid and essentially complete. MPA is metabolized to form the phenolic glucuronide of MPA (MPAG) which is not pharmacologically active. The parent drug, mycophenolate mofetil, can be measured systemically during the intravenous infusion; however, shortly (about 5 minutes) after the infusion is stopped or after oral administration, MMF concentration is below the limit of quantitation (0.4 µg/mL).

Absorption

In 12 healthy volunteers, the mean absolute bioavailability of oral mycophenolate mofetil relative to intravenous mycophenolate mofetil (based on MPA AUC) was 94%. The area under the plasma-concentration time curve (AUC) for MPA appears to increase in a dose-proportional fashion in renal transplant patients receiving multiple doses of mycophenolate mofetil up to a daily dose of 3 g (see Table 1).

Food (27 g fat, 650 calories) had no effect on the extent of absorption (MPA AUC) of mycophenolate mofetil when administered at doses of 1.5 g bid to renal transplant patients. However, MPA Cmax was decreased by 40% in the presence of food (see DOSAGE AND ADMINISTRATION).

Distribution

The mean (±SD) apparent volume of distribution of MPA in 12 healthy volunteers is approximately 3.6 (±1.5) and 4.0 (±1.2) L/kg following intravenous and oral administration, respectively. MPA, at clinically relevant concentrations, is 97% bound to plasma albumin. MPAG is 82% bound to plasma albumin at MPAG concentration ranges that are normally seen in stable renal transplant patients; however, at higher MPAG concentrations (observed in patients with renal impairment or delayed renal graft function), the binding of MPA may be reduced as a result of competition between MPAG and MPA for protein binding. Mean blood to plasma ratio of radioactivity concentrations was approximately 0.6 indicating that MPA and MPAG do not extensively distribute into the cellular fractions of blood.

In vitro studies to evaluate the effect of other agents on the binding of MPA to human serum albumin (HSA) or plasma proteins showed that salicylate (at 25 mg/dL with HSA) and MPAG (at ≥460 µg/mL with plasma proteins) increased the free fraction of MPA. At concentrations that exceeded what is encountered clinically, cyclosporine, digoxin, naproxen, prednisone, propranolol, tacrolimus, theophylline, tolbutamide, and warfarin did not increase the free fraction of MPA. MPA at concentrations as high as 100 µg/mL had little effect on the binding of warfarin, digoxin or propranolol, but decreased the binding of theophylline from 53% to 45% and phenytoin from 90% to 87%.

Metabolism

Following oral and intravenous dosing, mycophenolate mofetil undergoes complete metabolism to MPA, the active metabolite. Metabolism to MPA occurs presystemically after oral dosing. MPA is metabolized principally by glucuronyl transferase to form the phenolic glucuronide of MPA (MPAG) which is not pharmacologically active. In vivo, MPAG is converted to MPA via enterohepatic recirculation. The following metabolites of the 2-hydroxyethyl-morpholino moiety are also recovered in the urine following oral administration of mycophenolate mofetil to healthy subjects: N-(2-carboxymethyl)-morpholine, N-(2-hydroxyethyl)-morpholine, and the N-oxide of N-(2-hydroxyethyl)-morpholine.

Secondary peaks in the plasma MPA concentration-time profile are usually observed 6 to 12 hours postdose. The coadministration of cholestyramine (4 g tid) resulted in approximately a 40% decrease in the MPA AUC (largely as a consequence of lower concentrations in the terminal portion of the profile). These observations suggest that enterohepatic recirculation contributes to MPA plasma concentrations.

Increased plasma concentrations of mycophenolate mofetil metabolites (MPA 50% increase and MPAG about a 3-fold to 6-fold increase) are observed in patients with renal insufficiency (see CLINICAL PHARMACOLOGY: Special Populations).

Excretion

Negligible amount of drug is excreted as MPA (<1% of dose) in the urine. Orally administered radiolabeled mycophenolate mofetil resulted in complete recovery of the administered dose, with 93% of the administered dose recovered in the urine and 6% recovered in feces. Most (about 87%) of the administered dose is excreted in the urine as MPAG. At clinically encountered concentrations, MPA and MPAG are usually not removed by hemodialysis. However, at high MPAG plasma concentrations (>100 µg/mL), small amounts of MPAG are removed. Bile acid sequestrants, such as cholestyramine, reduce MPA AUC by interfering with enterohepatic circulation of the drug (see OVERDOSAGE).

Mean (±SD) apparent half-life and plasma clearance of MPA are 17.9 (±6.5) hours and 193 (±48) mL/min following oral administration and 16.6 (±5.8) hours and 177 (±31) mL/min following intravenous administration, respectively.

Pharmacokinetics in Healthy Volunteers, Renal, Cardiac, and Hepatic Transplant Patients

Shown below are the mean (±SD) pharmacokinetic parameters for MPA following the administration of mycophenolate mofetil given as single doses to healthy volunteers and multiple doses to renal, cardiac, and hepatic transplant patients. In the early posttransplant period (<40 days posttransplant), renal, cardiac, and hepatic transplant patients had mean MPA AUCs approximately 20% to 41% lower and mean Cmax approximately 32% to 44% lower compared to the late transplant period (3 to 6 months posttransplant).

Mean MPA AUC values following administration of 1 g bid intravenous mycophenolate mofetil over 2 hours to renal transplant patients for 5 days were about 24% higher than those observed after oral administration of a similar dose in the immediate posttransplant phase. In hepatic transplant patients, administration of 1 g bid intravenous CellCept followed by 1.5 g bid oral CellCept resulted in mean MPA AUC values similar to those found in renal transplant patients administered 1 g CellCept bid.

Table 1 Pharmacokinetic Parameters for MPA [mean (±SD)] Following Administration of Mycophenolate Mofetil to Healthy Volunteers (Single Dose), Renal, Cardiac, and Hepatic Transplant Patients (Multiple Doses)
 | Dose/Route | Tmax (h) | Cmax (µg/mL) | Total AUC (µg∙h/mL)
Healthy Volunteers (single dose) | 1 g/oral | 0.80 (±0.36) (n=129) | 24.5 (±9.5) (n=129) | 63.9 (±16.2) (n=117)
Renal Transplant Patients (bid dosing) Time After Transplantation | Dose/Route | Tmax (h) | Cmax (µg/mL) | Interdosing Interval AUC(0-12h) (µg∙h/mL)
5 days | 1 g/iv | 1.58 (±0.46) (n=31) | 12.0 (±3.82) (n=31) | 40.8 (±11.4) (n=31)
6 days | 1 g/oral | 1.33 (±1.05) (n=31) | 10.7 (±4.83) (n=31) | 32.9 (±15.0) (n=31)
Early (<40 days) | 1 g/oral | 1.31 (±0.76) (n=25) | 8.16 (±4.50) (n=25) | 27.3 (±10.9) (n=25)
Early (<40 days) | 1.5 g/oral | 1.21 (±0.81) (n=27) | 13.5 (±8.18) (n=27) | 38.4 (±15.4) (n=27)
Late (>3 months) | 1.5 g/oral | 0.90 (±0.24) (n=23) | 24.1 (±12.1) (n=23) | 65.3 (±35.4) (n=23)
Cardiac Transplant Patients (bid dosing) Time After Transplantation | Dose/Route | Tmax (h) | Cmax (µg/mL) | Interdosing Interval AUC(0-12h) (µg∙h/mL)
Early (Day before discharge) | 1.5 g/oral | 1.8 (±1.3) (n=11) | 11.5 (±6.8) (n=11) | 43.3 (±20.8) (n=9)
Late (>6 months) | 1.5 g/oral | 1.1 (±0.7) (n=52) | 20.0 (±9.4) (n=52) | 54.1 [AUC(0-12h) values quoted are extrapolated from data from samples collected over 4 hours.] (±20.4) (n=49)
Hepatic Transplant Patients (bid dosing) Time After Transplantation | Dose/Route | Tmax (h) | Cmax (µg/mL) | Interdosing Interval AUC(0-12h) (µg∙h/mL)
4 to 9 days | 1 g/iv | 1.50 (±0.517) (n=22) | 17.0 (±12.7) (n=22) | 34.0 (±17.4) (n=22)
Early (5 to 8 days) | 1.5 g/oral | 1.15 (±0.432) (n=20) | 13.1 (±6.76) (n=20) | 29.2 (±11.9) (n=20)
Late (>6 months) | 1.5 g/oral | 1.54 (±0.51) (n=6) | 19.3 (±11.7) (n=6) | 49.3 (±14.8) (n=6)

Two 500 mg tablets have been shown to be bioequivalent to four 250 mg capsules. Five mL of the 200 mg/mL constituted oral suspension have been shown to be bioequivalent to four 250 mg capsules.

Special Populations

Shown below are the mean (±SD) pharmacokinetic parameters for MPA following the administration of oral mycophenolate mofetil given as single doses to non-transplant subjects with renal or hepatic impairment.

Table 2 Pharmacokinetic Parameters for MPA [mean (±SD)] Following Single Doses of Mycophenolate Mofetil Capsules in Chronic Renal and Hepatic Impairment
Renal Impairment (no. of patients) | Dose | Tmax (h) | Cmax (µg/mL) | AUC(0-96h) (µg∙h/mL)
Healthy Volunteers GFR >80 mL/min/1.73 m^2 (n=6) | 1 g | 0.75 (±0.27) | 25.3 (±7.99) | 45.0 (±22.6)
Mild Renal Impairment GFR 50 to 80 mL/min/1.73 m^2 (n=6) | 1 g | 0.75 (±0.27) | 26.0 (±3.82) | 59.9 (±12.9)
Moderate Renal Impairment GFR 25 to 49 mL/min/1.73 m^2 (n=6) | 1 g | 0.75 (±0.27) | 19.0 (±13.2) | 52.9 (±25.5)
Severe Renal Impairment GFR <25 mL/min/1.73 m^2 (n=7) | 1 g | 1.00 (±0.41) | 16.3 (±10.8) | 78.6 (±46.4)
Hepatic Impairment (no. of patients) | Dose | Tmax (h) | Cmax (µg/mL) | AUC(0-48h) (µg∙h/mL)
Healthy Volunteers (n=6) | 1 g | 0.63 (±0.14) | 24.3 (±5.73) | 29.0 (±5.78)
Alcoholic Cirrhosis (n=18) | 1 g | 0.85 (±0.58) | 22.4 (±10.1) | 29.8 (±10.7)

Renal Insufficiency

In a single-dose study, MMF was administered as capsule or intravenous infusion over 40 minutes. Plasma MPA AUC observed after oral dosing to volunteers with severe chronic renal impairment [glomerular filtration rate (GFR) <25 mL/min/1.73 m^2] was about 75% higher relative to that observed in healthy volunteers (GFR >80 mL/min/1.73 m^2). In addition, the single-dose plasma MPAG AUC was 3-fold to 6-fold higher in volunteers with severe renal impairment than in volunteers with mild renal impairment or healthy volunteers, consistent with the known renal elimination of MPAG. No data are available on the safety of long-term exposure to this level of MPAG.

Plasma MPA AUC observed after single-dose (1 g) intravenous dosing to volunteers (n=4) with severe chronic renal impairment (GFR <25 mL/min/1.73 m^2) was 62.4 µg∙h/mL (±19.3). Multiple dosing of mycophenolate mofetil in patients with severe chronic renal impairment has not been studied (see PRECAUTIONS: General and DOSAGE AND ADMINISTRATION).

In patients with delayed renal graft function posttransplant, mean MPA AUC(0-12h) was comparable to that seen in posttransplant patients without delayed renal graft function. There is a potential for a transient increase in the free fraction and concentration of plasma MPA in patients with delayed renal graft function. However, dose adjustment does not appear to be necessary in patients with delayed renal graft function. Mean plasma MPAG AUC(0-12h) was 2-fold to 3-fold higher than in posttransplant patients without delayed renal graft function (see PRECAUTIONS: General and DOSAGE AND ADMINISTRATION).

In 8 patients with primary graft non-function following renal transplantation, plasma concentrations of MPAG accumulated about 6-fold to 8-fold after multiple dosing for 28 days. Accumulation of MPA was about 1-fold to 2-fold.

The pharmacokinetics of mycophenolate mofetil are not altered by hemodialysis. Hemodialysis usually does not remove MPA or MPAG. At high concentrations of MPAG (>100 µg/mL), hemodialysis removes only small amounts of MPAG.

Hepatic Insufficiency

In a single-dose (1 g oral) study of 18 volunteers with alcoholic cirrhosis and 6 healthy volunteers, hepatic MPA glucuronidation processes appeared to be relatively unaffected by hepatic parenchymal disease when pharmacokinetic parameters of healthy volunteers and alcoholic cirrhosis patients within this study were compared. However, it should be noted that for unexplained reasons, the healthy volunteers in this study had about a 50% lower AUC as compared to healthy volunteers in other studies, thus making comparisons between volunteers with alcoholic cirrhosis and healthy volunteers difficult. Effects of hepatic disease on this process probably depend on the particular disease. Hepatic disease with other etiologies, such as primary biliary cirrhosis, may show a different effect. In a single-dose (1 g intravenous) study of 6 volunteers with severe hepatic impairment (aminopyrine breath test less than 0.2% of dose) due to alcoholic cirrhosis, MMF was rapidly converted to MPA. MPA AUC was 44.1 µg∙h/mL (±15.5).

Pediatrics

The pharmacokinetic parameters of MPA and MPAG have been evaluated in 55 pediatric patients (ranging from 1 year to 18 years of age) receiving CellCept oral suspension at a dose of 600 mg/m^2 bid (up to a maximum of 1 g bid) after allogeneic renal transplantation. The pharmacokinetic data for MPA is provided in Table 3:

Table 3 Mean (±SD) Computed Pharmacokinetic Parameters for MPA by Age and Time After Allogeneic Renal Transplantation
Age Group | (n) | Time | Tmax (h) |  | Dose Adjusted [adjusted to a dose of 600 mg/m^2] Cmax (µg/mL) |  | Dose Adjusted AUC0-12 (µg∙h/mL)
 |  | Early (Day 7)
1 to <2 yr | (6) [a subset of 1 to <6 yr] |  | 3.03 | (4.70) | 10.3 | (5.80) | 22.5 | (6.66)
1 to <6 yr | (17) |  | 1.63 | (2.85) | 13.2 | (7.16) | 27.4 | (9.54)
6 to <12 yr | (16) |  | 0.940 | (0.546) | 13.1 | (6.30) | 33.2 | (12.1)
12 to 18 yr | (21) |  | 1.16 | (0.830) | 11.7 | (10.7) | 26.3 | (9.14) [n=20]
 |  | Late (Month 3)
1 to <2 yr | (4) |  | 0.725 | (0.276) | 23.8 | (13.4) | 47.4 | (14.7)
1 to <6 yr | (15) |  | 0.989 | (0.511) | 22.7 | (10.1) | 49.7 | (18.2)
6 to <12 yr | (14) |  | 1.21 | (0.532) | 27.8 | (14.3) | 61.9 | (19.6)
12 to 18 yr | (17) |  | 0.978 | (0.484) | 17.9 | (9.57) | 53.6 | (20.3) [n=16]
 |  | Late (Month 9)
1 to <2 yr | (4) |  | 0.604 | (0.208) | 25.6 | (4.25) | 55.8 | (11.6)
1 to <6 yr | (12) |  | 0.869 | (0.479) | 30.4 | (9.16) | 61.0 | (10.7)
6 to <12 yr | (11) |  | 1.12 | (0.462) | 29.2 | (12.6) | 66.8 | (21.2)
12 to 18 yr | (14) |  | 1.09 | (0.518) | 18.1 | (7.29) | 56.7 | (14.0)

The CellCept oral suspension dose of 600 mg/m^2 bid (up to a maximum of 1 g bid) achieved mean MPA AUC values in pediatric patients similar to those seen in adult renal transplant patients receiving CellCept capsules at a dose of 1 g bid in the early posttransplant period. There was wide variability in the data. As observed in adults, early posttransplant MPA AUC values were approximately 45% to 53% lower than those observed in the later posttransplant period (>3 months). MPA AUC values were similar in the early and late posttransplant period across the 1 year to 18 year age range.

Gender

Data obtained from several studies were pooled to look at any gender-related differences in the pharmacokinetics of MPA (data were adjusted to 1 g oral dose). Mean (±SD) MPA AUC(0-12h) for males (n=79) was 32.0 (±14.5) and for females (n=41) was 36.5 (±18.8) µg∙h/mL while mean (±SD) MPA Cmax was 9.96 (±6.19) in the males and 10.6 (±5.64) µg/mL in the females. These differences are not of clinical significance.

Geriatrics

Pharmacokinetics in the elderly have not been studied.

CLINICAL STUDIES

Adults

The safety and efficacy of CellCept in combination with corticosteroids and cyclosporine for the prevention of organ rejection were assessed in randomized, double-blind, multicenter trials in renal (3 trials), in cardiac (1 trial), and in hepatic (1 trial) adult transplant patients.

Renal Transplant

Adults

The three renal studies compared two dose levels of oral CellCept (1 g bid and 1.5 g bid) with azathioprine (2 studies) or placebo (1 study) when administered in combination with cyclosporine (Sandimmune®) and corticosteroids to prevent acute rejection episodes. One study also included antithymocyte globulin (ATGAM®) induction therapy. These studies are described by geographic location of the investigational sites. One study was conducted in the USA at 14 sites, one study was conducted in Europe at 20 sites, and one study was conducted in Europe, Canada, and Australia at a total of 21 sites.

The primary efficacy endpoint was the proportion of patients in each treatment group who experienced treatment failure within the first 6 months after transplantation (defined as biopsy-proven acute rejection on treatment or the occurrence of death, graft loss or early termination from the study for any reason without prior biopsy-proven rejection). CellCept, when administered with antithymocyte globulin (ATGAM®) induction (one study) and with cyclosporine and corticosteroids (all three studies), was compared to the following three therapeutic regimens: (1) antithymocyte globulin (ATGAM®) induction/azathioprine/cyclosporine/corticosteroids, (2) azathioprine/cyclosporine/corticosteroids, and (3) cyclosporine/corticosteroids.

CellCept, in combination with corticosteroids and cyclosporine reduced (statistically significant at 0.05 level) the incidence of treatment failure within the first 6 months following transplantation. Table 4 and Table 5 summarize the results of these studies. These tables show (1) the proportion of patients experiencing treatment failure, (2) the proportion of patients who experienced biopsy-proven acute rejection on treatment, and (3) early termination, for any reason other than graft loss or death, without a prior biopsy-proven acute rejection episode. Patients who prematurely discontinued treatment were followed for the occurrence of death or graft loss, and the cumulative incidence of graft loss and patient death are summarized separately. Patients who prematurely discontinued treatment were not followed for the occurrence of acute rejection after termination. More patients receiving CellCept discontinued without prior biopsy-proven rejection, death or graft loss than discontinued in the control groups, with the highest rate in the CellCept 3 g/day group. Therefore, the acute rejection rates may be underestimates, particularly in the CellCept 3 g/day group.

Table 4 Renal Transplant Studies
Incidence of Treatment Failure (Biopsy-proven Rejection or Early Termination for Any Reason)
USA Study [Antithymocyte globulin induction/MMF or azathioprine/cyclosporine/corticosteroids.] (N=499 patients) | CellCept 2 g/day (n=167 patients) | CellCept 3 g/day (n=166 patients) | Azathioprine 1 to 2 mg/kg/day (n=166 patients)
All treatment failures | 31.1% | 31.3% | 47.6%
Early termination without prior acute rejection [Does not include death and graft loss as reason for early termination.] | 9.6% | 12.7% | 6.0%
Biopsy-proven rejection episode on treatment | 19.8% | 17.5% | 38.0%
Europe/Canada/ Australia Study [MMF or azathioprine/cyclosporine/corticosteroids.] (N=503 patients) | CellCept 2 g/day (n=173 patients) | CellCept 3 g/day (n=164 patients) | Azathioprine 100 to 150 mg/day (n=166 patients)
All treatment failures | 38.2% | 34.8% | 50.0%
Early termination without prior acute rejection | 13.9% | 15.2% | 10.2%
Biopsy-proven rejection episode on treatment | 19.7% | 15.9% | 35.5%
Europe Study [MMF or placebo/cyclosporine/corticosteroids.] (N=491 patients) | CellCept 2 g/day (n=165 patients) | CellCept 3 g/day (n=160 patients) | Placebo (n=166 patients)
All treatment failures | 30.3% | 38.8% | 56.0%
Early termination without prior acute rejection | 11.5% | 22.5% | 7.2%
Biopsy-proven rejection episode on treatment | 17.0% | 13.8% | 46.4%

The cumulative incidence of 12-month graft loss or patient death is presented below. No advantage of CellCept with respect to graft loss or patient death was established. Numerically, patients receiving CellCept 2 g/day and 3 g/day experienced a better outcome than controls in all three studies; patients receiving CellCept 2 g/day experienced a better outcome than CellCept 3 g/day in two of the three studies. Patients in all treatment groups who terminated treatment early were found to have a poor outcome with respect to graft loss or patient death at 1 year.

Table 5 Renal Transplant Studies
Cumulative Incidence of Combined Graft Loss or Patient Death at 12 Months
Study | CellCept 2 g/day | CellCept 3 g/day | Control (Azathioprine or Placebo)
USA | 8.5% | 11.5% | 12.2%
Europe/Canada/Australia | 11.7% | 11.0% | 13.6%
Europe | 8.5% | 10.0% | 11.5%

Pediatrics

One open-label, safety and pharmacokinetic study of CellCept oral suspension 600 mg/m^2 bid (up to 1 g bid) in combination with cyclosporine and corticosteroids was performed at centers in the US (9), Europe (5) and Australia (1) in 100 pediatric patients (3 months to 18 years of age) for the prevention of renal allograft rejection. CellCept was well tolerated in pediatric patients (see ADVERSE REACTIONS), and the pharmacokinetics profile was similar to that seen in adult patients dosed with 1 g bid CellCept capsules (see CLINICAL PHARMACOLOGY: Pharmacokinetics). The rate of biopsy-proven rejection was similar across the age groups (3 months to <6 years, 6 years to <12 years, 12 years to 18 years). The overall biopsy-proven rejection rate at 6 months was comparable to adults. The combined incidence of graft loss (5%) and patient death (2%) at 12 months posttransplant was similar to that observed in adult renal transplant patients.

Cardiac Transplant

A double-blind, randomized, comparative, parallel-group, multicenter study in primary cardiac transplant recipients was performed at 20 centers in the United States, 1 in Canada, 5 in Europe and 2 in Australia. The total number of patients enrolled was 650; 72 never received study drug and 578 received study drug. Patients received CellCept 1.5 g bid (n=289) or azathioprine 1.5 to 3 mg/kg/day (n=289), in combination with cyclosporine (Sandimmune® or Neoral®) and corticosteroids as maintenance immunosuppressive therapy. The two primary efficacy endpoints were: (1) the proportion of patients who, after transplantation, had at least one endomyocardial biopsy-proven rejection with hemodynamic compromise, or were retransplanted or died, within the first 6 months, and (2) the proportion of patients who died or were retransplanted during the first 12 months following transplantation. Patients who prematurely discontinued treatment were followed for the occurrence of allograft rejection for up to 6 months and for the occurrence of death for 1 year.

(1) Rejection: No difference was established between CellCept and azathioprine (AZA) with respect to biopsy-proven rejection with hemodynamic compromise.

(2) Survival: CellCept was shown to be at least as effective as AZA in preventing death or retransplantation at 1 year (see Table 6).

Table 6 Rejection at 6 Months/Death or Retransplantation at 1 Year
 | All Patients |  | Treated Patients
 | AZA N = 323 | CellCept N = 327 | AZA N = 289 | CellCept N = 289
Biopsy-proven rejection with hemodynamic compromise at 6 months [Hemodynamic compromise occurred if any of the following criteria were met: pulmonary capillary wedge pressure ≥20 mm or a 25% increase; cardiac index <2.0 L/min/m^2 or a 25% decrease; ejection fraction ≤30%; pulmonary artery oxygen saturation ≤60% or a 25% decrease; presence of new S3 gallop; fractional shortening was ≤20% or a 25% decrease; inotropic support required to manage the clinical condition.] | 121 (38%) | 120 (37%) | 100 (35%) | 92 (32%)
Death or retransplantation at 1 year | 49 (15.2%) | 42 (12.8%) | 33 (11.4%) | 18 (6.2%)

Hepatic Transplant

A double-blind, randomized, comparative, parallel-group, multicenter study in primary hepatic transplant recipients was performed at 16 centers in the United States, 2 in Canada, 4 in Europe and 1 in Australia. The total number of patients enrolled was 565. Per protocol, patients received CellCept 1 g bid intravenously for up to 14 days followed by CellCept 1.5 g bid orally or azathioprine 1 to 2 mg/kg/day intravenously followed by azathioprine 1 to 2 mg/kg/day orally, in combination with cyclosporine (Neoral®) and corticosteroids as maintenance immunosuppressive therapy. The actual median oral dose of azathioprine on study was 1.5 mg/kg/day (range of 0.3 to 3.8 mg/kg/day) initially and 1.26 mg/kg/day (range of 0.3 to 3.8 mg/kg/day) at 12 months. The two primary endpoints were: (1) the proportion of patients who experienced, in the first 6 months posttransplantation, one or more episodes of biopsy-proven and treated rejection or death or retransplantation, and (2) the proportion of patients who experienced graft loss (death or retransplantation) during the first 12 months posttransplantation. Patients who prematurely discontinued treatment were followed for the occurrence of allograft rejection and for the occurrence of graft loss (death or retransplantation) for 1 year.

Results

In combination with corticosteroids and cyclosporine, CellCept obtained a lower rate of acute rejection at 6 months and a similar rate of death or retransplantation at 1 year compared to azathioprine.

Table 7 Rejection at 6 Months/Death or Retransplantation at 1 Year
 | AZA N = 287 | CellCept N = 278
Biopsy-proven, treated rejection at 6 months (includes death or retransplantation) | 137 (47.7%) | 107 (38.5%)
Death or retransplantation at 1 year | 42 (14.6%) | 41 (14.7%)

INDICATIONS AND USAGE

Renal, Cardiac, and Hepatic Transplant

CellCept is indicated for the prophylaxis of organ rejection in patients receiving allogeneic renal, cardiac or hepatic transplants. CellCept should be used concomitantly with cyclosporine and corticosteroids.

CellCept Intravenous is an alternative dosage form to CellCept capsules, tablets and oral suspension. CellCept Intravenous should be administered within 24 hours following transplantation. CellCept Intravenous can be administered for up to 14 days; patients should be switched to oral CellCept as soon as they can tolerate oral medication.

CONTRAINDICATIONS

Allergic reactions to CellCept have been observed; therefore, CellCept is contraindicated in patients with a hypersensitivity to mycophenolate mofetil, mycophenolic acid or any component of the drug product. CellCept Intravenous is contraindicated in patients who are allergic to Polysorbate 80 (TWEEN).

WARNINGS

(see boxed WARNING)

Lymphoma and Malignancy

Patients receiving immunosuppressive regimens involving combinations of drugs, including CellCept, as part of an immunosuppressive regimen are at increased risk of developing lymphomas and other malignancies, particularly of the skin (see ADVERSE REACTIONS). The risk appears to be related to the intensity and duration of immunosuppression rather than to the use of any specific agent.

As usual for patients with increased risk for skin cancer, exposure to sunlight and UV light should be limited by wearing protective clothing and using a sunscreen with a high protection factor.

Lymphoproliferative disease or lymphoma developed in 0.4% to 1% of patients receiving CellCept (2 g or 3 g) with other immunosuppressive agents in controlled clinical trials of renal, cardiac, and hepatic transplant patients (see ADVERSE REACTIONS).

In pediatric patients, no other malignancies besides lymphoproliferative disorder (2/148 patients) have been observed (see ADVERSE REACTIONS).

Combination with Other Immunosuppressive Agents

CellCept has been administered in combination with the following agents in clinical trials: antithymocyte globulin (ATGAM®), OKT3 (Orthoclone OKT® 3), cyclosporine (Sandimmune®, Neoral®) and corticosteroids. The efficacy and safety of the use of CellCept in combination with other immunosuppressive agents have not been determined.

Infections

Oversuppression of the immune system can also increase susceptibility to infection, including opportunistic infections, fatal infections, and sepsis. In patients receiving CellCept (2 g or 3 g) in controlled studies for prevention of renal, cardiac or hepatic rejection, fatal infection/sepsis occurred in approximately 2% of renal and cardiac patients and in 5% of hepatic patients (see ADVERSE REACTIONS).

Latent Viral Infections

Immunosuppressed patients are at increased risk for opportunistic infections, including activation of latent viral infections. These include cases of progressive multifocal leukoencephalopathy (PML) and BK virus-associated nephropathy (BKVAN) which have been observed in patients receiving immunosuppressants, including CellCept.

Cases of progressive multifocal leukoencephalopathy (PML), sometimes fatal, have been reported in patients treated with CellCept. Hemiparesis, apathy, confusion, cognitive deficiencies and ataxia were the most frequent clinical features observed. The reported cases generally had risk factors for PML, including treatment with immunosuppressant therapies and impairment of immune function. In immunosuppressed patients, physicians should consider PML in the differential diagnosis in patients reporting neurological symptoms and consultation with a neurologist should be considered as clinically indicated. Consideration should be given to reducing the amount of immunosuppression in patients who develop PML. In transplant patients, physicians should also consider the risk that reduced immunosuppression represents to the graft.

BKVAN is associated with serious outcomes, including deteriorating renal function and renal graft loss (see ADVERSE REACTIONS: Postmarketing Experience). Patient monitoring may help detect patients at risk for BK virus-associated nephropathy. Reduction in immunosuppression should be considered for patients who develop evidence of BK virus-associated nephropathy.

Pregnancy

Teratogenic Effects

Pregnancy Category D

Mycophenolate mofetil (MMF) can cause fetal harm when administered to a pregnant woman. Use of MMF during pregnancy is associated with an increased risk of first trimester pregnancy loss and an increased risk of congenital malformations, especially external ear and other facial abnormalities including cleft lip and palate, and anomalies of the distal limbs, heart, esophagus, and kidney. In the National Transplantation Pregnancy Registry (NTPR), there were data on 33 MMF-exposed pregnancies in 24 transplant patients; there were 15 spontaneous abortions (45%) and 18 live-born infants. Four of these 18 infants had structural malformations (22%). In postmarketing data (collected 1995-2007) on 77 women exposed to systemic MMF during pregnancy, 25 had spontaneous abortions and 14 had a malformed infant or fetus. Six of 14 malformed offspring had ear abnormalities. Because these postmarketing data are reported voluntarily, it is not always possible to reliably estimate the frequency of particular adverse outcomes. These malformations seen in offspring were similar to findings in animal reproductive toxicology studies. For comparison, the background rate for congenital anomalies in the United States is about 3%, and NTPR data show a rate of 4-5% among babies born to organ transplant patients using other immunosuppressive drugs.

In animal reproductive toxicology studies, there were increased rates of fetal resorptions and malformations in the absence of maternal toxicity. Female rats and rabbits received mycophenolate mofetil (MMF) doses equivalent to 0.02 to 0.9 times the recommended human dose for renal and cardiac transplant patients, based on body surface area conversions. In rat offspring, malformations included anophthalmia, agnathia, and hydrocephaly. In rabbit offspring, malformations included ectopia cordis, ectopic kidneys, diaphragmatic hernia, and umbilical hernia.

If this drug is used during pregnancy, or if the patient becomes pregnant while taking this drug, the patient should be apprised of the potential hazard to the fetus. In certain situations, the patient and her healthcare practitioner may decide that the maternal benefits outweigh the risks to the fetus. Women using CellCept at any time during pregnancy should be encouraged to enroll in the National Transplantation Pregnancy Registry.

Pregnancy Exposure Prevention

Women of childbearing potential should have a negative serum or urine pregnancy test with a sensitivity of at least 25 mIU/mL within 1 week prior to beginning therapy. CellCept therapy should not be initiated until a negative pregnancy test report is obtained.

Women of childbearing potential (including pubertal girls and peri-menopausal women) taking CellCept must receive contraceptive counseling and use effective contraception. The patient should begin using her two chosen methods of contraception 4 weeks prior to starting CellCept therapy, unless abstinence is the chosen method. She should continue contraceptive use during therapy and for 6 weeks after stopping CellCept. Patients should be aware that CellCept reduces blood levels of the hormones in the oral contraceptive pill and could theoretically reduce its effectiveness (see PRECAUTIONS: Information for Patients and PRECAUTIONS: Drug Interactions: Oral Contraceptives).

Neutropenia

Severe neutropenia [absolute neutrophil count (ANC) <0.5 × 10^3/µL] developed in up to 2.0% of renal, up to 2.8% of cardiac, and up to 3.6% of hepatic transplant patients receiving CellCept 3 g daily (see ADVERSE REACTIONS). Patients receiving CellCept should be monitored for neutropenia (see PRECAUTIONS: Laboratory Tests). The development of neutropenia may be related to CellCept itself, concomitant medications, viral infections, or some combination of these causes. If neutropenia develops (ANC <1.3 × 10^3/µL), dosing with CellCept should be interrupted or the dose reduced, appropriate diagnostic tests performed, and the patient managed appropriately (see DOSAGE AND ADMINISTRATION). Neutropenia has been observed most frequently in the period from 31 to 180 days posttransplant in patients treated for prevention of renal, cardiac, and hepatic rejection.

Patients receiving CellCept should be instructed to report immediately any evidence of infection, unexpected bruising, bleeding or any other manifestation of bone marrow depression.

Pure Red Cell Aplasia (PRCA)

Cases of pure red cell aplasia (PRCA) have been reported in patients treated with CellCept in combination with other immunosuppressive agents. The mechanism for mycophenolate mofetil induced PRCA is unknown; the relative contribution of other immunosuppressants and their combinations in an immunosuppression regimen are also unknown. In some cases, PRCA was found to be reversible with dose reduction or cessation of CellCept therapy. In transplant patients, however, reduced immunosuppression may place the graft at risk.

CAUTION: CELLCEPT INTRAVENOUS SOLUTION SHOULD NEVER BE ADMINISTERED BY RAPID OR BOLUS INTRAVENOUS INJECTION.

PRECAUTIONS

General

Gastrointestinal bleeding (requiring hospitalization) has been observed in approximately 3% of renal, in 1.7% of cardiac, and in 5.4% of hepatic transplant patients treated with CellCept 3 g daily. In pediatric renal transplant patients, 5/148 cases of gastrointestinal bleeding (requiring hospitalization) were observed.

Gastrointestinal perforations have rarely been observed. Most patients receiving CellCept were also receiving other drugs known to be associated with these complications. Patients with active peptic ulcer disease were excluded from enrollment in studies with mycophenolate mofetil. Because CellCept has been associated with an increased incidence of digestive system adverse events, including infrequent cases of gastrointestinal tract ulceration, hemorrhage, and perforation, CellCept should be administered with caution in patients with active serious digestive system disease.

Subjects with severe chronic renal impairment (GFR <25 mL/min/1.73 m^2) who have received single doses of CellCept showed higher plasma MPA and MPAG AUCs relative to subjects with lesser degrees of renal impairment or normal healthy volunteers. No data are available on the safety of long-term exposure to these levels of MPAG. Doses of CellCept greater than 1 g administered twice a day to renal transplant patients should be avoided and they should be carefully observed (see CLINICAL PHARMACOLOGY: Pharmacokinetics and DOSAGE AND ADMINISTRATION).

No data are available for cardiac or hepatic transplant patients with severe chronic renal impairment. CellCept may be used for cardiac or hepatic transplant patients with severe chronic renal impairment if the potential benefits outweigh the potential risks.

In patients with delayed renal graft function posttransplant, mean MPA AUC(0-12h) was comparable, but MPAG AUC(0-12h) was 2-fold to 3-fold higher, compared to that seen in posttransplant patients without delayed renal graft function. In the three controlled studies of prevention of renal rejection, there were 298 of 1483 patients (20%) with delayed graft function. Although patients with delayed graft function have a higher incidence of certain adverse events (anemia, thrombocytopenia, hyperkalemia) than patients without delayed graft function, these events were not more frequent in patients receiving CellCept than azathioprine or placebo. No dose adjustment is recommended for these patients; however, they should be carefully observed (see CLINICAL PHARMACOLOGY: Pharmacokinetics and DOSAGE AND ADMINISTRATION).

In cardiac transplant patients, the overall incidence of opportunistic infections was approximately 10% higher in patients treated with CellCept than in those receiving azathioprine therapy, but this difference was not associated with excess mortality due to infection/sepsis among patients treated with CellCept (see ADVERSE REACTIONS).

There were more herpes virus (H. simplex, H. zoster, and cytomegalovirus) infections in cardiac transplant patients treated with CellCept compared to those treated with azathioprine (see ADVERSE REACTIONS).

It is recommended that CellCept not be administered concomitantly with azathioprine because both have the potential to cause bone marrow suppression and such concomitant administration has not been studied clinically.

In view of the significant reduction in the AUC of MPA by cholestyramine, caution should be used in the concomitant administration of CellCept with drugs that interfere with enterohepatic recirculation because of the potential to reduce the efficacy of CellCept (see PRECAUTIONS: Drug Interactions).

On theoretical grounds, because CellCept is an IMPDH (inosine monophosphate dehydrogenase) inhibitor, it should be avoided in patients with rare hereditary deficiency of hypoxanthine-guanine phosphoribosyl-transferase (HGPRT) such as Lesch-Nyhan and Kelley-Seegmiller syndrome.

During treatment with CellCept, the use of live attenuated vaccines should be avoided and patients should be advised that vaccinations may be less effective (see PRECAUTIONS: Drug Interactions: Live Vaccines).

Phenylketonurics

CellCept Oral Suspension contains aspartame, a source of phenylalanine (0.56 mg phenylalanine/mL suspension). Therefore, care should be taken if CellCept Oral Suspension is administered to patients with phenylketonuria.

Information for Patients

- Give patients complete dosage instructions and inform them about the increased risk of lymphoproliferative disease and certain other malignancies.
- Inform patients that they need repeated appropriate laboratory tests while they are taking CellCept.
- Inform women of childbearing potential that use of CellCept in pregnancy is associated with an increased risk of first trimester pregnancy loss and an increased risk of birth defects, and that they must use effective contraception.
- Discuss pregnancy plans with female patients of childbearing potential.
  - ♦Any female of childbearing potential must use highly effective (two methods) contraception 4 weeks prior to starting CellCept therapy and continue contraception until 6 weeks after stopping CellCept treatment, unless abstinence is the chosen method (see WARNINGS: Pregnancy).
  - ♦A patient who is planning a pregnancy should not use CellCept unless she cannot be successfully treated with other immunosuppressant drugs.

Laboratory Tests

Complete blood counts should be performed weekly during the first month, twice monthly for the second and third months of treatment, then monthly through the first year (see WARNINGS, ADVERSE REACTIONS and DOSAGE AND ADMINISTRATION).

Drug Interactions

Drug interaction studies with mycophenolate mofetil have been conducted with acyclovir, antacids, cholestyramine, cyclosporine, ganciclovir, oral contraceptives, sevelamer, trimethoprim/sulfamethoxazole, norfloxacin, and metronidazole. Drug interaction studies have not been conducted with other drugs that may be commonly administered to renal, cardiac or hepatic transplant patients. CellCept has not been administered concomitantly with azathioprine.

Acyclovir

Coadministration of mycophenolate mofetil (1 g) and acyclovir (800 mg) to 12 healthy volunteers resulted in no significant change in MPA AUC and Cmax. However, MPAG and acyclovir plasma AUCs were increased 10.6% and 21.9%, respectively. Because MPAG plasma concentrations are increased in the presence of renal impairment, as are acyclovir concentrations, the potential exists for mycophenolate and acyclovir or its prodrug (eg, valacyclovir) to compete for tubular secretion, further increasing the concentrations of both drugs.

Antacids With Magnesium and Aluminum Hydroxides

Absorption of a single dose of mycophenolate mofetil (2 g) was decreased when administered to ten rheumatoid arthritis patients also taking Maalox® TC (10 mL qid). The Cmax and AUC(0-24h) for MPA were 33% and 17% lower, respectively, than when mycophenolate mofetil was administered alone under fasting conditions. CellCept may be administered to patients who are also taking antacids containing magnesium and aluminum hydroxides; however, it is recommended that CellCept and the antacid not be administered simultaneously.

Cholestyramine

Following single-dose administration of 1.5 g mycophenolate mofetil to 12 healthy volunteers pretreated with 4 g tid of cholestyramine for 4 days, MPA AUC decreased approximately 40%. This decrease is consistent with interruption of enterohepatic recirculation which may be due to binding of recirculating MPAG with cholestyramine in the intestine. Some degree of enterohepatic recirculation is also anticipated following intravenous administration of CellCept. Therefore, CellCept is not recommended to be given with cholestyramine or other agents that may interfere with enterohepatic recirculation.

Cyclosporine

Cyclosporine (Sandimmune®) pharmacokinetics (at doses of 275 to 415 mg/day) were unaffected by single and multiple doses of 1.5 g bid of mycophenolate mofetil in 10 stable renal transplant patients. The mean (±SD) AUC(0-12h) and Cmax of cyclosporine after 14 days of multiple doses of mycophenolate mofetil were 3290 (±822) ng∙h/mL and 753 (±161) ng/mL, respectively, compared to 3245 (±1088) ng∙h/mL and 700 (±246) ng/mL, respectively, 1 week before administration of mycophenolate mofetil.

In renal transplant patients, mean MPA exposure (AUC0-12h) was approximately 30-50% greater when mycophenolate mofetil is administered without cyclosporine compared with when mycophenolate mofetil is coadministered with cyclosporine. This interaction is due to cyclosporine inhibition of multidrug-resistance-associated protein 2 (MRP-2) transporter in the biliary tract, thereby preventing the excretion of MPAG into the bile that would lead to enterohepatic recirculation of MPA. This information should be taken into consideration when MMF is used without cyclosporine.

Ganciclovir

Following single-dose administration to 12 stable renal transplant patients, no pharmacokinetic interaction was observed between mycophenolate mofetil (1.5 g) and intravenous ganciclovir (5 mg/kg). Mean (±SD) ganciclovir AUC and Cmax (n=10) were 54.3 (±19.0) µg∙h/mL and 11.5 (±1.8) µg/mL, respectively, after coadministration of the two drugs, compared to 51.0 (±17.0) µg∙h/mL and 10.6 (±2.0) µg/mL, respectively, after administration of intravenous ganciclovir alone. The mean (±SD) AUC and Cmax of MPA (n=12) after coadministration were 80.9 (±21.6) µg∙h/mL and 27.8 (±13.9) µg/mL, respectively, compared to values of 80.3 (±16.4) µg∙h/mL and 30.9 (±11.2) µg/mL, respectively, after administration of mycophenolate mofetil alone. Because MPAG plasma concentrations are increased in the presence of renal impairment, as are ganciclovir concentrations, the two drugs will compete for tubular secretion and thus further increases in concentrations of both drugs may occur. In patients with renal impairment in which MMF and ganciclovir or its prodrug (eg, valganciclovir) are coadministered, patients should be monitored carefully.

Oral Contraceptives

A study of coadministration of CellCept (1 g bid) and combined oral contraceptives containing ethinylestradiol (0.02 mg to 0.04 mg) and levonorgestrel (0.05 mg to 0.20 mg), desogestrel (0.15 mg) or gestodene (0.05 mg to 0.10 mg) was conducted in 18 women with psoriasis over 3 consecutive menstrual cycles. Mean AUC(0-24h) was similar for ethinylestradiol and 3-keto desogestrel; however, mean levonorgestrel AUC(0-24h) significantly decreased by about 15%. There was large inter-patient variability (%CV in the range of 60% to 70%) in the data, especially for ethinylestradiol. Mean serum levels of LH, FSH and progesterone were not significantly affected. CellCept may not have any influence on the ovulation-suppressing action of the studied oral contraceptives. However, it is recommended that oral contraceptives are coadministered with CellCept with caution and additional birth control methods be considered (see WARNINGS: Pregnancy).

Sevelamer

Concomitant administration of sevelamer and mycophenolate mofetil in adult and pediatric patients decreased the mean MPA Cmax and AUC0-12h by 36% and 26% respectively. This data suggest that sevelamer and other calcium free phosphate binders should not be administered simultaneously with CellCept. Alternatively, it is recommended that sevelamer and other calcium free phosphate binders preferentially could be given 2 hours after CellCept intake to minimize the impact on the absorption of MPA.

Trimethoprim/sulfamethoxazole

Following single-dose administration of mycophenolate mofetil (1.5 g) to 12 healthy male volunteers on day 8 of a 10 day course of trimethoprim 160 mg/sulfamethoxazole 800 mg administered bid, no effect on the bioavailability of MPA was observed. The mean (±SD) AUC and Cmax of MPA after concomitant administration were 75.2 (±19.8) µg∙h/mL and 34.0 (±6.6) µg/mL, respectively, compared to 79.2 (±27.9) µg∙h/mL and 34.2 (±10.7) µg/mL, respectively, after administration of mycophenolate mofetil alone.

Norfloxacin and Metronidazole

Following single-dose administration of mycophenolate mofetil (1 g) to 11 healthy volunteers on day 4 of a 5 day course of a combination of norfloxacin and metronidazole, the mean MPA AUC0-48h was significantly reduced by 33% compared to the administration of mycophenolate mofetil alone (p<0.05). Therefore, CellCept is not recommended to be given with the combination of norfloxacin and metronidazole. There was no significant effect on mean MPA AUC0-48h when mycophenolate mofetil was concomitantly administered with norfloxacin or metronidazole separately. The mean (±SD) MPA AUC0-48h after coadministration of mycophenolate mofetil with norfloxacin or metronidazole separately was 48.3 (±24) µg∙h/mL and 42.7 (±23) µg∙h/mL, respectively, compared with 56.2 (±24) µg∙h/mL after administration of mycophenolate mofetil alone.

Ciprofloxacin and Amoxicillin plus Clavulanic Acid

A total of 64 CellCept-treated renal transplant recipients received either oral ciprofloxacin 500 mg bid or amoxicillin plus clavulanic acid 375 mg tid for 7 or at least 14 days. Approximately 50% reductions in median trough MPA concentrations (pre-dose) from baseline (CellCept alone) were observed in 3 days following commencement of oral ciprofloxacin or amoxicillin plus clavulanic acid. These reductions in trough MPA concentrations tended to diminish within 14 days of antibiotic therapy and ceased within 3 days after discontinuation of antibiotics. The postulated mechanism for this interaction is an antibiotic-induced reduction in glucuronidase-possessing enteric organisms leading to a decrease in enterohepatic recirculation of MPA. The change in trough level may not accurately represent changes in overall MPA exposure; therefore, clinical relevance of these observations is unclear.

Rifampin

In a single heart-lung transplant patient, after correction for dose, a 67% decrease in MPA exposure (AUC0-12h) has been observed with concomitant administration of mycophenolate mofetil and rifampin. Therefore, CellCept is not recommended to be given with rifampin concomitantly unless the benefit outweighs the risk.

Other Interactions

The measured value for renal clearance of MPAG indicates removal occurs by renal tubular secretion as well as glomerular filtration. Consistent with this, coadministration of probenecid, a known inhibitor of tubular secretion, with mycophenolate mofetil in monkeys results in a 3-fold increase in plasma MPAG AUC and a 2-fold increase in plasma MPA AUC. Thus, other drugs known to undergo renal tubular secretion may compete with MPAG and thereby raise plasma concentrations of MPAG or the other drug undergoing tubular secretion.

Drugs that alter the gastrointestinal flora may interact with mycophenolate mofetil by disrupting enterohepatic recirculation. Interference of MPAG hydrolysis may lead to less MPA available for absorption.

Live Vaccines

During treatment with CellCept, the use of live attenuated vaccines should be avoided and patients should be advised that vaccinations may be less effective (see PRECAUTIONS: General). Influenza vaccination may be of value. Prescribers should refer to national guidelines for influenza vaccination.

Carcinogenesis, Mutagenesis, Impairment of Fertility

In a 104-week oral carcinogenicity study in mice, mycophenolate mofetil in daily doses up to 180 mg/kg was not tumorigenic. The highest dose tested was 0.5 times the recommended clinical dose (2 g/day) in renal transplant patients and 0.3 times the recommended clinical dose (3 g/day) in cardiac transplant patients when corrected for differences in body surface area (BSA). In a 104-week oral carcinogenicity study in rats, mycophenolate mofetil in daily doses up to 15 mg/kg was not tumorigenic. The highest dose was 0.08 times the recommended clinical dose in renal transplant patients and 0.05 times the recommended clinical dose in cardiac transplant patients when corrected for BSA. While these animal doses were lower than those given to patients, they were maximal in those species and were considered adequate to evaluate the potential for human risk (see WARNINGS).

The genotoxic potential of mycophenolate mofetil was determined in five assays. Mycophenolate mofetil was genotoxic in the mouse lymphoma/thymidine kinase assay and the in vivo mouse micronucleus assay. Mycophenolate mofetil was not genotoxic in the bacterial mutation assay, the yeast mitotic gene conversion assay or the Chinese hamster ovary cell chromosomal aberration assay.

Mycophenolate mofetil had no effect on fertility of male rats at oral doses up to 20 mg/kg/day. This dose represents 0.1 times the recommended clinical dose in renal transplant patients and 0.07 times the recommended clinical dose in cardiac transplant patients when corrected for BSA. In a female fertility and reproduction study conducted in rats, oral doses of 4.5 mg/kg/day caused malformations (principally of the head and eyes) in the first generation offspring in the absence of maternal toxicity. This dose was 0.02 times the recommended clinical dose in renal transplant patients and 0.01 times the recommended clinical dose in cardiac transplant patients when corrected for BSA. No effects on fertility or reproductive parameters were evident in the dams or in the subsequent generation.

Pregnancy

Teratogenic Effects

Pregnancy Category D

See WARNINGS section.

Nursing Mothers

Studies in rats treated with mycophenolate mofetil have shown mycophenolic acid to be excreted in milk. It is not known whether this drug is excreted in human milk. Because many drugs are excreted in human milk, and because of the potential for serious adverse reactions in nursing infants from mycophenolate mofetil, a decision should be made whether to discontinue nursing or to discontinue the drug, taking into account the importance of the drug to the mother.

Pediatric Use

Based on pharmacokinetic and safety data in pediatric patients after renal transplantation, the recommended dose of CellCept oral suspension is 600 mg/m^2 bid (up to a maximum of 1 g bid). Also see CLINICAL PHARMACOLOGY, CLINICAL STUDIES, ADVERSE REACTIONS, and DOSAGE AND ADMINISTRATION.

Safety and effectiveness in pediatric patients receiving allogeneic cardiac or hepatic transplants have not been established.

Geriatric Use

Clinical studies of CellCept did not include sufficient numbers of subjects aged 65 and over to determine whether they respond differently from younger subjects. Other reported clinical experience has not identified differences in responses between the elderly and younger patients. In general dose selection for an elderly patient should be cautious, reflecting the greater frequency of decreased hepatic, renal or cardiac function and of concomitant or other drug therapy. Elderly patients may be at an increased risk of adverse reactions compared with younger individuals (see ADVERSE REACTIONS).

ADVERSE REACTIONS

The principal adverse reactions associated with the administration of CellCept include diarrhea, leukopenia, sepsis, vomiting, and there is evidence of a higher frequency of certain types of infections eg, opportunistic infection (see WARNINGS: Infections and WARNINGS: Latent Viral Infections). The adverse event profile associated with the administration of CellCept Intravenous has been shown to be similar to that observed after administration of oral dosage forms of CellCept.

CellCept Oral

The incidence of adverse events for CellCept was determined in randomized, comparative, double-blind trials in prevention of rejection in renal (2 active, 1 placebo-controlled trials), cardiac (1 active-controlled trial), and hepatic (1 active-controlled trial) transplant patients.

Geriatrics

Elderly patients (≥65 years), particularly those who are receiving CellCept as part of a combination immunosuppressive regimen, may be at increased risk of certain infections (including cytomegalovirus [CMV] tissue invasive disease) and possibly gastrointestinal hemorrhage and pulmonary edema, compared to younger individuals (see PRECAUTIONS).

Safety data are summarized below for all active-controlled trials in renal (2 trials), cardiac (1 trial), and hepatic (1 trial) transplant patients. Approximately 53% of the renal patients, 65% of the cardiac patients, and 48% of the hepatic patients have been treated for more than 1 year. Adverse events reported in ≥20% of patients in the CellCept treatment groups are presented below.

Table 8 Adverse Events in Controlled Studies in Prevention of Renal, Cardiac or Hepatic Allograft Rejection (Reported in ≥20% of Patients in the CellCept Group)
 | Renal Studies |  |  | Cardiac Study |  | Hepatic Study
 | CellCept 2 g/day | CellCept 3 g/day | Azathioprine 1 to 2 mg/kg/day or 100 to 150 mg/day | CellCept 3 g/day | Azathioprine 1.5 to 3 mg/kg/day | CellCept 3 g/day | Azathioprine 1 to 2 mg/kg/day
 | (n=336) | (n=330) | (n=326) | (n=289) | (n=289) | (n=277) | (n=287)
 | % | % | % | % | % | % | %
Body as a Whole
Pain | 33.0 | 31.2 | 32.2 | 75.8 | 74.7 | 74.0 | 77.7
Abdominal pain | 24.7 | 27.6 | 23.0 | 33.9 | 33.2 | 62.5 | 51.2
Fever | 21.4 | 23.3 | 23.3 | 47.4 | 46.4 | 52.3 | 56.1
Headache | 21.1 | 16.1 | 21.2 | 54.3 | 51.9 | 53.8 | 49.1
Infection | 18.2 | 20.9 | 19.9 | 25.6 | 19.4 | 27.1 | 25.1
Sepsis | – | – | – | – | – | 27.4 | 26.5
Asthenia | – | – | – | 43.3 | 36.3 | 35.4 | 33.8
Chest pain | – | – | – | 26.3 | 26.0 | – | –
Back pain | – | – | – | 34.6 | 28.4 | 46.6 | 47.4
Ascites | – | – | – | – | – | 24.2 | 22.6
Hematologic and Lymphatic
Anemia | 25.6 | 25.8 | 23.6 | 42.9 | 43.9 | 43.0 | 53.0
Leukopenia | 23.2 | 34.5 | 24.8 | 30.4 | 39.1 | 45.8 | 39.0
Thrombocytopenia | – | – | – | 23.5 | 27.0 | 38.3 | 42.2
Hypochromic anemia | – | – | – | 24.6 | 23.5 | – | –
Leukocytosis | – | – | – | 40.5 | 35.6 | 22.4 | 21.3
Urogenital
Urinary tract infection | 37.2 | 37.0 | 33.7 | – | – | – | –
Kidney function abnormal | – | – | – | 21.8 | 26.3 | 25.6 | 28.9
Cardiovascular
Hypertension | 32.4 | 28.2 | 32.2 | 77.5 | 72.3 | 62.1 | 59.6
Hypotension | – | – | – | 32.5 | 36.0 | – | –
Cardiovascular disorder | – | – | – | 25.6 | 24.2 | – | –
Tachycardia | – | – | – | 20.1 | 18.0 | 22.0 | 15.7
Metabolic and Nutritional
Peripheral edema | 28.6 | 27.0 | 28.2 | 64.0 | 53.3 | 48.4 | 47.7
Hyper-cholesteremia | – | – | – | 41.2 | 38.4 | – | –
Edema | – | – | – | 26.6 | 25.6 | 28.2 | 28.2
Hypokalemia | – | – | – | 31.8 | 25.6 | 37.2 | 41.1
Hyperkalemia | – | – | – | – | – | 22.0 | 23.7
Hyperglycemia | – | – | – | 46.7 | 52.6 | 43.7 | 48.8
Creatinine increased | – | – | – | 39.4 | 36.0 | – | –
BUN increased | – | – | – | 34.6 | 32.5 | – | –
Lactic dehydrogenase increased | – | – | – | 23.2 | 17.0 | – | –
Hypomagnesemia | – | – | – | – | – | 39.0 | 37.6
Hypocalcemia | – | – | – | – | – | 30.0 | 30.0
Digestive
Diarrhea | 31.0 | 36.1 | 20.9 | 45.3 | 34.3 | 51.3 | 49.8
Constipation | 22.9 | 18.5 | 22.4 | 41.2 | 37.7 | 37.9 | 38.3
Nausea | 19.9 | 23.6 | 24.5 | 54.0 | 54.3 | 54.5 | 51.2
Dyspepsia | – | – | – | – | – | 22.4 | 20.9
Vomiting | – | – | – | 33.9 | 28.4 | 32.9 | 33.4
Anorexia | – | – | – | – | – | 25.3 | 17.1
Liver function tests abnormal | – | – | – | – | – | 24.9 | 19.2
Respiratory
Infection | 22.0 | 23.9 | 19.6 | 37.0 | 35.3 | – | –
Dyspnea | – | – | – | 36.7 | 36.3 | 31.0 | 30.3
Cough increased | – | – | – | 31.1 | 25.6 | – | –
Lung disorder | – | – | – | 30.1 | 29.1 | 22.0 | 18.8
Sinusitis | – | – | – | 26.0 | 19.0 | – | –
Pleural effusion | – | – | – | – | – | 34.3 | 35.9
Skin and Appendages
Rash | – | – | – | 22.1 | 18.0 | – | –
Nervous System
Tremor | – | – | – | 24.2 | 23.9 | 33.9 | 35.5
Insomnia | – | – | – | 40.8 | 37.7 | 52.3 | 47.0
Dizziness | – | – | – | 28.7 | 27.7 | – | –
Anxiety | – | – | – | 28.4 | 23.9 | – | –
Paresthesia | – | – | – | 20.8 | 18.0 | – | –

The placebo-controlled renal transplant study generally showed fewer adverse events occurring in ≥20% of patients. In addition, those that occurred were not only qualitatively similar to the azathioprine-controlled renal transplant studies, but also occurred at lower rates, particularly for infection, leukopenia, hypertension, diarrhea and respiratory infection.

The above data demonstrate that in three controlled trials for prevention of renal rejection, patients receiving 2 g/day of CellCept had an overall better safety profile than did patients receiving 3 g/day of CellCept.

The above data demonstrate that the types of adverse events observed in multicenter controlled trials in renal, cardiac, and hepatic transplant patients are qualitatively similar except for those that are unique to the specific organ involved.

Sepsis, which was generally CMV viremia, was slightly more common in renal transplant patients treated with CellCept compared to patients treated with azathioprine. The incidence of sepsis was comparable in CellCept and in azathioprine-treated patients in cardiac and hepatic studies.

In the digestive system, diarrhea was increased in renal and cardiac transplant patients receiving CellCept compared to patients receiving azathioprine, but was comparable in hepatic transplant patients treated with CellCept or azathioprine.

Patients receiving CellCept alone or as part of an immunosuppressive regimen are at increased risk of developing lymphomas and other malignancies, particularly of the skin (see WARNINGS: Lymphoma and Malignancy). The incidence of malignancies among the 1483 patients treated in controlled trials for the prevention of renal allograft rejection who were followed for ≥1 year was similar to the incidence reported in the literature for renal allograft recipients.

Lymphoproliferative disease or lymphoma developed in 0.4% to 1% of patients receiving CellCept (2 g or 3 g daily) with other immunosuppressive agents in controlled clinical trials of renal, cardiac, and hepatic transplant patients followed for at least 1 year (see WARNINGS: Lymphoma and Malignancy). Non-melanoma skin carcinomas occurred in 1.6% to 4.2% of patients, other types of malignancy in 0.7% to 2.1% of patients. Three-year safety data in renal and cardiac transplant patients did not reveal any unexpected changes in incidence of malignancy compared to the 1-year data.

In pediatric patients, no other malignancies besides lymphoproliferative disorder (2/148 patients) have been observed.

Severe neutropenia (ANC <0.5 × 10^3/µL) developed in up to 2.0% of renal transplant patients, up to 2.8% of cardiac transplant patients and up to 3.6% of hepatic transplant patients receiving CellCept 3 g daily (see WARNINGS: Neutropenia, PRECAUTIONS: Laboratory Tests and DOSAGE AND ADMINISTRATION).

All transplant patients are at increased risk of opportunistic infections. The risk increases with total immunosuppressive load (see WARNINGS: Infections and WARNINGS: Latent Viral Infections). Table 9 shows the incidence of opportunistic infections that occurred in the renal, cardiac, and hepatic transplant populations in the azathioprine-controlled prevention trials:

Table 9 Viral and Fungal Infections in Controlled Studies in Prevention of Renal, Cardiac or Hepatic Transplant Rejection
 | Renal Studies |  |  | Cardiac Study |  | Hepatic Study
 | CellCept 2 g/day | CellCept 3 g/day | Azathioprine 1 to 2 mg/kg/day or 100 to 150 mg/day | CellCept 3 g/day | Azathioprine 1.5 to 3 mg/kg/day | CellCept 3 g/day | Azathioprine 1 to 2 mg/kg/day
 | (n=336) | (n=330) | (n=326) | (n=289) | (n=289) | (n=277) | (n=287)
 | % | % | % | % | % | % | %
Herpes simplex | 16.7 | 20.0 | 19.0 | 20.8 | 14.5 | 10.1 | 5.9
CMV
– Viremia/ syndrome | 13.4 | 12.4 | 13.8 | 12.1 | 10.0 | 14.1 | 12.2
– Tissue invasive disease | 8.3 | 11.5 | 6.1 | 11.4 | 8.7 | 5.8 | 8.0
Herpes zoster | 6.0 | 7.6 | 5.8 | 10.7 | 5.9 | 4.3 | 4.9
– Cutaneous disease | 6.0 | 7.3 | 5.5 | 10.0 | 5.5 | 4.3 | 4.9
Candida | 17.0 | 17.3 | 18.1 | 18.7 | 17.6 | 22.4 | 24.4
– Mucocutaneous | 15.5 | 16.4 | 15.3 | 18.0 | 17.3 | 18.4 | 17.4

The following other opportunistic infections occurred with an incidence of less than 4% in CellCept patients in the above azathioprine-controlled studies: Herpes zoster, visceral disease; Candida, urinary tract infection, fungemia/disseminated disease, tissue invasive disease; Cryptococcosis; Aspergillus/Mucor; Pneumocystis carinii.

In the placebo-controlled renal transplant study, the same pattern of opportunistic infection was observed compared to the azathioprine-controlled renal studies, with a notably lower incidence of the following: Herpes simplex and CMV tissue-invasive disease.

In patients receiving CellCept (2 g or 3 g) in controlled studies for prevention of renal, cardiac or hepatic rejection, fatal infection/sepsis occurred in approximately 2% of renal and cardiac patients and in 5% of hepatic patients (see WARNINGS: Infections).

In cardiac transplant patients, the overall incidence of opportunistic infections was approximately 10% higher in patients treated with CellCept than in those receiving azathioprine, but this difference was not associated with excess mortality due to infection/sepsis among patients treated with CellCept.

The following adverse events were reported with 3% to <20% incidence in renal, cardiac, and hepatic transplant patients treated with CellCept, in combination with cyclosporine and corticosteroids.

Table 10 Adverse Events Reported in 3% to <20% of Patients Treated With CellCept in Combination With Cyclosporine and Corticosteroids
Body System
Body as a Whole | abdomen enlarged, abscess, accidental injury, cellulitis, chills occurring with fever, cyst, face edema, flu syndrome, hemorrhage, hernia, lab test abnormal, malaise, neck pain, pelvic pain, peritonitis
Hematologic and Lymphatic | coagulation disorder, ecchymosis, pancytopenia, petechia, polycythemia, prothrombin time increased, thromboplastin time increased
Urogenital | acute kidney failure, albuminuria, dysuria, hydronephrosis, hematuria, impotence, kidney failure, kidney tubular necrosis, nocturia, oliguria, pain, prostatic disorder, pyelonephritis, scrotal edema, urine abnormality, urinary frequency, urinary incontinence, urinary retention, urinary tract disorder
Cardiovascular | angina pectoris, arrhythmia, arterial thrombosis, atrial fibrillation, atrial flutter, bradycardia, cardiovascular disorder, congestive heart failure, extrasystole, heart arrest, heart failure, hypotension, pallor, palpitation, pericardial effusion, peripheral vascular disorder, postural hypotension, pulmonary hypertension, supraventricular tachycardia, supraventricular extrasystoles, syncope, tachycardia, thrombosis, vasodilatation, vasospasm, ventricular extrasystole, ventricular tachycardia, venous pressure increased
Metabolic and Nutritional | abnormal healing, acidosis, alkaline phosphatase increased, alkalosis, bilirubinemia, creatinine increased, dehydration, gamma glutamyl transpeptidase increased, generalized edema, gout, hypercalcemia, hypercholesteremia, hyperlipemia, hyperphosphatemia, hyperuricemia, hypervolemia, hypocalcemia, hypochloremia, hypoglycemia, hyponatremia, hypophosphatemia, hypoproteinemia, hypovolemia, hypoxia, lactic dehydrogenase increased, respiratory acidosis, SGOT increased, SGPT increased, thirst, weight gain, weight loss
Digestive | anorexia, cholangitis, cholestatic jaundice, dysphagia, esophagitis, flatulence, gastritis, gastroenteritis, gastrointestinal disorder, gastrointestinal hemorrhage, gastrointestinal moniliasis, gingivitis, gum hyperplasia, hepatitis, ileus, infection, jaundice, liver damage, liver function tests abnormal, melena, mouth ulceration, nausea and vomiting, oral moniliasis, rectal disorder, stomach ulcer, stomatitis
Respiratory | apnea, asthma, atelectasis, bronchitis, epistaxis, hemoptysis, hiccup, hyperventilation, lung edema, lung disorder, neoplasm, pain, pharyngitis, pleural effusion, pneumonia, pneumothorax, respiratory disorder, respiratory moniliasis, rhinitis, sinusitis, sputum increased, voice alteration
Skin and Appendages | acne, alopecia, fungal dermatitis, hemorrhage, hirsutism, pruritus, rash, skin benign neoplasm, skin carcinoma, skin disorder, skin hypertrophy, skin ulcer, sweating, vesiculobullous rash
Nervous | agitation, anxiety, confusion, convulsion, delirium, depression, dry mouth, emotional lability, hallucinations, hypertonia, hypesthesia, nervousness, neuropathy, paresthesia, psychosis, somnolence, thinking abnormal, vertigo
Endocrine | Cushing's syndrome, diabetes mellitus, hypothyroidism, parathyroid disorder
Musculoskeletal | arthralgia, joint disorder, leg cramps, myalgia, myasthenia, osteoporosis
Special Senses | abnormal vision, amblyopia, cataract (not specified), conjunctivitis, deafness, ear disorder, ear pain, eye hemorrhage, tinnitus, lacrimation disorder

Pediatrics

The type and frequency of adverse events in a clinical study in 100 pediatric patients 3 months to 18 years of age dosed with CellCept oral suspension 600 mg/m^2 bid (up to 1 g bid) were generally similar to those observed in adult patients dosed with CellCept capsules at a dose of 1 g bid with the exception of abdominal pain, fever, infection, pain, sepsis, diarrhea, vomiting, pharyngitis, respiratory tract infection, hypertension, leukopenia, and anemia, which were observed in a higher proportion in pediatric patients.

CellCept Intravenous

The adverse event profile of CellCept Intravenous was determined from a single, double-blind, controlled comparative study of the safety of 2 g/day of intravenous and oral CellCept in renal transplant patients in the immediate posttransplant period (administered for the first 5 days). The potential venous irritation of CellCept Intravenous was evaluated by comparing the adverse events attributable to peripheral venous infusion of CellCept Intravenous with those observed in the intravenous placebo group; patients in this group received active medication by the oral route.

Adverse events attributable to peripheral venous infusion were phlebitis and thrombosis, both observed at 4% in patients treated with CellCept Intravenous.

In the active controlled study in hepatic transplant patients, 2 g/day of CellCept Intravenous were administered in the immediate posttransplant period (up to 14 days). The safety profile of intravenous CellCept was similar to that of intravenous azathioprine.

Postmarketing Experience

Congenital Disorders

Congenital malformations including ear malformations have been reported in offspring of patients exposed to mycophenolate mofetil during pregnancy (see WARNINGS: Pregnancy).

Digestive

Colitis (sometimes caused by cytomegalovirus), pancreatitis, isolated cases of intestinal villous atrophy.

Hematologic and Lymphatic

Cases of pure red cell aplasia (PRCA) have been reported in patients treated with CellCept in combination with other immunosuppressive agents.

Infections

Serious life-threatening infections such as meningitis and infectious endocarditis have been reported occasionally and there is evidence of a higher frequency of certain types of serious infections such as tuberculosis and atypical mycobacterial infection. Cases of progressive multifocal leukoencephalopathy (PML), sometimes fatal, have been reported in patients treated with CellCept. The reported cases generally had risk factors for PML, including treatment with immunosuppressant therapies and impairment of immune function. BK virus-associated nephropathy has been observed in patients receiving immunosuppressants, including CellCept. This infection is associated with serious outcomes, including deteriorating renal function and renal graft loss.

Respiratory

Interstitial lung disorders, including fatal pulmonary fibrosis, have been reported rarely and should be considered in the differential diagnosis of pulmonary symptoms ranging from dyspnea to respiratory failure in posttransplant patients receiving CellCept.

OVERDOSAGE

The experience with overdose of CellCept in humans is very limited. The events received from reports of overdose fall within the known safety profile of the drug. The highest dose administered to renal transplant patients in clinical trials has been 4 g/day. In limited experience with cardiac and hepatic transplant patients in clinical trials, the highest doses used were 4 g/day or 5 g/day. At doses of 4 g/day or 5 g/day, there appears to be a higher rate, compared to the use of 3 g/day or less, of gastrointestinal intolerance (nausea, vomiting, and/or diarrhea), and occasional hematologic abnormalities, principally neutropenia, leading to a need to reduce or discontinue dosing.

In acute oral toxicity studies, no deaths occurred in adult mice at doses up to 4000 mg/kg or in adult monkeys at doses up to 1000 mg/kg; these were the highest doses of mycophenolate mofetil tested in these species. These doses represent 11 times the recommended clinical dose in renal transplant patients and approximately 7 times the recommended clinical dose in cardiac transplant patients when corrected for BSA. In adult rats, deaths occurred after single-oral doses of 500 mg/kg of mycophenolate mofetil. The dose represents approximately 3 times the recommended clinical dose in cardiac transplant patients when corrected for BSA.

MPA and MPAG are usually not removed by hemodialysis. However, at high MPAG plasma concentrations (>100 µg/mL), small amounts of MPAG are removed. By increasing excretion of the drug, MPA can be removed by bile acid sequestrants, such as cholestyramine (see CLINICAL PHARMACOLOGY: Pharmacokinetics).

DOSAGE AND ADMINISTRATION

Renal Transplantation

Adults

A dose of 1 g administered orally or intravenously (over NO LESS THAN 2 HOURS) twice a day (daily dose of 2 g) is recommended for use in renal transplant patients. Although a dose of 1.5 g administered twice daily (daily dose of 3 g) was used in clinical trials and was shown to be safe and effective, no efficacy advantage could be established for renal transplant patients. Patients receiving 2 g/day of CellCept demonstrated an overall better safety profile than did patients receiving 3 g/day of CellCept.

Pediatrics (3 months to 18 years of age)

The recommended dose of CellCept oral suspension is 600 mg/m^2 administered twice daily (up to a maximum daily dose of 2 g/10 mL oral suspension). Patients with a body surface area of 1.25 m^2 to 1.5 m^2 may be dosed with CellCept capsules at a dose of 750 mg twice daily (1.5 g daily dose). Patients with a body surface area >1.5 m^2 may be dosed with CellCept capsules or tablets at a dose of 1 g twice daily (2 g daily dose).

Cardiac Transplantation

Adults

A dose of 1.5 g bid administered intravenously (over NO LESS THAN 2 HOURS) or 1.5 g bid oral (daily dose of 3 g) is recommended for use in adult cardiac transplant patients.

Hepatic Transplantation

Adults

A dose of 1 g bid administered intravenously (over NO LESS THAN 2 HOURS) or 1.5 g bid oral (daily dose of 3 g) is recommended for use in adult hepatic transplant patients.

CellCept Capsules, Tablets, and Oral Suspension

The initial oral dose of CellCept should be given as soon as possible following renal, cardiac or hepatic transplantation. Food had no effect on MPA AUC, but has been shown to decrease MPA Cmax by 40%. Therefore, it is recommended that CellCept be administered on an empty stomach. However, in stable renal transplant patients, CellCept may be administered with food if necessary.

Note:
If required, CellCept Oral Suspension can be administered via a nasogastric tube with a minimum size of 8 French (minimum 1.7 mm interior diameter).

Patients With Hepatic Impairment

No dose adjustments are recommended for renal patients with severe hepatic parenchymal disease. However, it is not known whether dose adjustments are needed for hepatic disease with other etiologies (see CLINICAL PHARMACOLOGY: Pharmacokinetics).

No data are available for cardiac transplant patients with severe hepatic parenchymal disease.

Geriatrics

The recommended oral dose of 1 g bid for renal transplant patients, 1.5 g bid for cardiac transplant patients, and 1 g bid administered intravenously or 1.5 g bid administered orally in hepatic transplant patients is appropriate for elderly patients (see PRECAUTIONS: Geriatric Use).

Preparation of Oral Suspension

It is recommended that CellCept Oral Suspension be constituted by the pharmacist prior to dispensing to the patient.

CellCept Oral Suspension should not be mixed with any other medication.

Mycophenolate mofetil has demonstrated teratogenic effects in rats and rabbits. There are no adequate and well-controlled studies in pregnant women (see WARNINGS, PRECAUTIONS, ADVERSE REACTIONS, and HANDLING AND DISPOSAL). Care should be taken to avoid inhalation or direct contact with skin or mucous membranes of the dry powder or the constituted suspension. If such contact occurs, wash thoroughly with soap and water; rinse eyes with water.

1. Tap the closed bottle several times to loosen the powder.
2. Measure 94 mL of water in a graduated cylinder.
3. Add approximately half the total amount of water for constitution to the bottle and shake the closed bottle well for about 1 minute.
4. Add the remainder of water and shake the closed bottle well for about 1 minute.
5. Remove the child-resistant cap and push bottle adapter into neck of bottle.
6. Close bottle with child-resistant cap tightly. This will assure the proper seating of the bottle adapter in the bottle and child-resistant status of the cap.

Dispense with patient instruction sheet and oral dispensers. It is recommended to write the date of expiration of the constituted suspension on the bottle label. (The shelf-life of the constituted suspension is 60 days.)

After constitution the oral suspension contains 200 mg/mL mycophenolate mofetil. Store constituted suspension at 25°C (77°F); excursions permitted to 15° to 30°C (59° to 86°F). Storage in a refrigerator at 2° to 8°C (36° to 46°F) is acceptable. Do not freeze. Discard any unused portion 60 days after constitution.

CellCept Intravenous

Adults

CellCept Intravenous is an alternative dosage form to CellCept capsules, tablets and oral suspension recommended for patients unable to take oral CellCept. CellCept Intravenous should be administered within 24 hours following transplantation. CellCept Intravenous can be administered for up to 14 days; patients should be switched to oral CellCept as soon as they can tolerate oral medication.

CellCept Intravenous must be reconstituted and diluted to a concentration of 6 mg/mL using 5% Dextrose Injection USP. CellCept Intravenous is incompatible with other intravenous infusion solutions. Following reconstitution, CellCept Intravenous must be administered by slow intravenous infusion over a period of NO LESS THAN 2 HOURS by either peripheral or central vein.

CAUTION: CELLCEPT INTRAVENOUS SOLUTION SHOULD NEVER BE ADMINISTERED BY RAPID OR BOLUS INTRAVENOUS INJECTION (see WARNINGS).

Preparation of Infusion Solution (6 mg/mL)

Caution should be exercised in the handling and preparation of solutions of CellCept Intravenous. Avoid direct contact of the prepared solution of CellCept Intravenous with skin or mucous membranes. If such contact occurs, wash thoroughly with soap and water; rinse eyes with plain water (see WARNINGS, PRECAUTIONS, ADVERSE REACTIONS, and HANDLING AND DISPOSAL).

CellCept Intravenous does not contain an antibacterial preservative; therefore, reconstitution and dilution of the product must be performed under aseptic conditions. Additionally, this product is sealed under vacuum and should retain a vacuum throughout its shelf life. If a lack of vacuum in the vial is noted while adding diluent, the vial should not be used.

CellCept Intravenous infusion solution must be prepared in two steps: the first step is a reconstitution step with 5% Dextrose Injection USP, and the second step is a dilution step with 5% Dextrose Injection USP. A detailed description of the preparation is given below:

Step 1

- a)Two (2) vials of CellCept Intravenous are used for preparing each 1 g dose, whereas three (3) vials are needed for each 1.5 g dose. Reconstitute the contents of each vial by injecting 14 mL of 5% Dextrose Injection USP.
- b)Gently shake the vial to dissolve the drug.
- c)Inspect the resulting slightly yellow solution for particulate matter and discoloration prior to further dilution. Discard the vials if particulate matter or discoloration is observed.

Step 2

- a)To prepare a 1 g dose, further dilute the contents of the two reconstituted vials (approx. 2 × 15 mL) into 140 mL of 5% Dextrose Injection USP. To prepare a 1.5 g dose, further dilute the contents of the three reconstituted vials (approx. 3 × 15 mL) into 210 mL of 5% Dextrose Injection USP. The final concentration of both solutions is 6 mg mycophenolate mofetil per mL.
- b)Inspect the infusion solution for particulate matter or discoloration. Discard the infusion solution if particulate matter or discoloration is observed.

If the infusion solution is not prepared immediately prior to administration, the commencement of administration of the infusion solution should be within 4 hours from reconstitution and dilution of the drug product. Keep solutions at 25°C (77°F); excursions permitted to 15° to 30°C (59° to 86°F).

CellCept Intravenous should not be mixed or administered concurrently via the same infusion catheter with other intravenous drugs or infusion admixtures.

Dosage Adjustments

In renal transplant patients with severe chronic renal impairment (GFR <25 mL/min/1.73 m^2) outside the immediate posttransplant period, doses of CellCept greater than 1 g administered twice a day should be avoided. These patients should also be carefully observed. No dose adjustments are needed in renal transplant patients experiencing delayed graft function postoperatively (see CLINICAL PHARMACOLOGY: Pharmacokinetics and PRECAUTIONS: General).

No data are available for cardiac or hepatic transplant patients with severe chronic renal impairment. CellCept may be used for cardiac or hepatic transplant patients with severe chronic renal impairment if the potential benefits outweigh the potential risks.

If neutropenia develops (ANC <1.3 × 10^3/µL), dosing with CellCept should be interrupted or the dose reduced, appropriate diagnostic tests performed, and the patient managed appropriately (see WARNINGS: Neutropenia, ADVERSE REACTIONS, and PRECAUTIONS: Laboratory Tests).

HANDLING AND DISPOSAL

Mycophenolate mofetil has demonstrated teratogenic effects in rats and rabbits (see WARNINGS: Pregnancy). CellCept tablets should not be crushed and CellCept capsules should not be opened or crushed. Avoid inhalation or direct contact with skin or mucous membranes of the powder contained in CellCept capsules and CellCept Oral Suspension (before or after constitution). If such contact occurs, wash thoroughly with soap and water; rinse eyes with plain water. Should a spill occur, wipe up using paper towels wetted with water to remove spilled powder or suspension. Caution should be exercised in the handling and preparation of solutions of CellCept Intravenous. Avoid direct contact of the prepared solution of CellCept Intravenous with skin or mucous membranes. If such contact occurs, wash thoroughly with soap and water; rinse eyes with plain water.

HOW SUPPLIED

CellCept (mycophenolate mofetil capsules) 250 mg

Blue-brown, two-piece hard gelatin capsules, printed in black with "CellCept 250" on the blue cap and "Roche" on the brown body. Supplied in the following presentations:

NDC Number | Size
NDC 21695-171-00 | Bottle of 100

Storage and Dispensing Information

Store at 25°C (77°F); excursions permitted to 15° to 30°C (59° to 86°F). Dispense in light-resistant containers, such as the manufacturer's original containers.

MEDICATION GUIDE

CellCept® [SEL-sept]
(mycophenolate mofetil capsules)
(mycophenolate mofetil tablets)

CellCept® Oral Suspension
(mycophenolate mofetil for oral suspension)

CellCept® Intravenous
(mycophenolate mofetil hydrochloride for injection)

Read the Medication Guide that comes with CellCept before you start taking it and each time you refill your prescription. There may be new information. This Medication Guide does not take the place of talking with your healthcare provider about your medical condition or your treatment.

What is the most important information I should know about CellCept?

CellCept can cause serious side effects:

- Possible loss of a pregnancy and higher risk of birth defects. Women who take CellCept during pregnancy have a higher risk of losing a pregnancy (miscarriage) during the first 3 months (first trimester), and a higher risk that their baby will be born with birth defects
  If you are a female and are able to become pregnant
  - your healthcare provider must talk with you about effective birth control methods (contraceptive counseling)
  - you should have a negative pregnancy test within 1 week before you start to take CellCept
  - you must use 2 different types of effective birth control at the same time, for 4 weeks before you start taking CellCept, during your entire CellCept therapy and for 6 weeks after stopping CellCept, unless you choose to avoid sexual intercourse completely (abstinence). CellCept decreases blood levels of the hormones in birth control pills that you take by mouth. Birth control pills may not work as well while you take CellCept, and you could become pregnant
    If you plan to become pregnant, talk with your healthcare provider. Your healthcare provider will decide if other medicines to prevent rejection may be right for you. In certain situations, you and your healthcare provider may decide that taking CellCept is more important to your health than the possible risks to your unborn baby.

- If you get pregnant while taking CellCept, do not stop taking CellCept. Call your healthcare provider right away. You and your healthcare provider should report any cases of pregnancies to
  - FDA MedWatch at 1-800-FDA-1088
  - Genentech at 1-888-835-2555
  Talk to your healthcare provider about joining the National Transplantation Pregnancy Registry at 1-877-955-6877.

- Increased risk of getting serious infections. CellCept weakens the body's immune system and affects your ability to fight infections. Serious infections can happen with CellCept and can lead to death. Types of infections can include:
  - Viral infections. Certain viruses can live in your body and cause active infections when your immune system is weak. Viral infections that can happen with CellCept include:
    - Shingles, other herpes infections, and cytomegalovirus (CMV). CMV can cause serious tissue and blood infections.
    - BK virus. BK virus can affect how your kidney works and cause your transplanted kidney to fail.
  - A brain infection called Progressive Multifocal Leukoencephalopathy (PML). In some patients, CellCept may cause an infection of the brain that may cause death. You are at risk for this brain infection because you have a weakened immune system. You should tell your healthcare provider right away if you have any of the following symptoms:
    - Weakness on one side of the body
    - You do not care about things that you usually care about (apathy)
    - You are confused or have problems thinking
    - You can not control your muscles
  - Fungal infections. Yeasts and other types of fungal infections can happen with CellCept and can cause serious tissue and blood infections (see "What are the possible side effects of CellCept?")

Call your healthcare provider right away if you have any of the following signs and symptoms of infection:

- Temperature of 100.5°F or greater
- Cold symptoms, such as a runny nose or sore throat
- Flu symptoms, such as an upset stomach, stomach pain, vomiting or diarrhea
- Earache or headache
- Pain during urination
- White patches in the mouth or throat
- Unexpected bruising or bleeding
- Cuts, scrapes or incisions that are red, warm and oozing pus

- Increased risk of getting certain cancers. People who take CellCept have a higher risk of getting lymphoma, and other cancers, especially skin cancer. Tell your healthcare provider if you have:
  - unexplained fever, prolonged tiredness, weight loss or lymph node swelling
  - a brown or black skin lesion with uneven borders, or one part of the lesion does not look like the other
  - a change in the size and color of a mole
  - a new skin lesion or bump
  - any other changes to your health

See the section "What are the possible side effects of CellCept?" for information about other serious side effects.

What is CellCept?

CellCept is a prescription medicine to prevent rejection (antirejection medicine) in people who have received a kidney, heart or liver transplant. Rejection is when the body's immune system perceives the new organ as a "foreign" threat and attacks it.

CellCept is used with other medicines called cyclosporine (Sandimmune®, Gengraf®, Neoral®) and corticosteroids. These medicines work together to prevent rejection to your transplanted organ.

CellCept has been used safely and works in children who received a kidney transplant as it does in adults. It is not known if CellCept is safe and works in children who receive a heart or liver transplant.

Who should not take CellCept?

Do not take CellCept if you are allergic to mycophenolate mofetil or any of the ingredients in CellCept. See the end of this Medication Guide for a complete list of ingredients in CellCept.

What should I tell my healthcare provider before taking CellCept?

Tell your healthcare provider about all of your medical conditions, if you:

- have any digestive problems, such as ulcers
- have Phenylketonuria (PKU). CellCept oral suspension contains aspartame (a source of phenylalanine)
- have Lesch-Nyhan or Kelley-Seegmiller syndrome or another rare inherited deficiency hypoxanthine-guanine phosphoribosyl-transferase (HGPRT). You should not take CellCept if you have one of these disorders
- plan to receive any vaccines. People taking CellCept should not take live vaccines. Some vaccines may not work as well during treatment with CellCept
- are pregnant or are planning to become pregnant. See "What is the most important information I should know about CellCept?"
- are breastfeeding. It is not known if CellCept passes into breast milk. You and your healthcare provider will decide if you will take CellCept or breastfeed. You should not do both without first talking with your healthcare provider

Tell your healthcare provider about all of the medicines you are taking including prescription and nonprescription medicines, vitamins and herbal supplements. Some medicines may affect the way CellCept works, and CellCept may affect how some medicines work. Especially tell your healthcare provider if you take:

- birth control pills (oral contraceptives). See "What is the most important information I should know about CellCept?"
- sevelamer (Renagel®, Renvela™). These products should be taken 2 hours after taking CellCept
- acyclovir (Zovirax®), valacyclovir (Valtrex®), ganciclovir (CYTOVENE®-IV, Vitrasert®), valganciclovir (VALCYTE®)
- rifampin (Rifater®, Rifamate®, Rimactane®, Rifadin®)
- antacids that contain magnesium and aluminum (CellCept and the antacid should not be taken at the same time)
- sulfamethoxazole/trimethoprim (BACTRIM™, BACTRIM DS™)
- norfloxacin (Noroxin®) and metronidazole (Flagyl®, Flagyl® ER, Flagyl® IV, Metro IV, Helidac®, Pylera™)
- ciprofloxacin (Cipro®, Cipro® XR, Ciloxan®, Proquin® XR) and amoxicillin plus clavulanic acid (Augmentin®, Augmentin XR™)
- azathioprine (Azasan®, Imuran®)
- cholestyramine (Questran Light®, Questran®, Locholest Light, Locholest, Prevalite®)

Know the medicines you take. Keep a list of them to show to your healthcare provider and pharmacist when you get a new medicine. Do not take any new medicine without talking with your healthcare provider.

How should I take CellCept?

- Take CellCept exactly as prescribed
- Do not stop taking CellCept or change the dose unless your healthcare provider tells you to
- If you miss a dose of CellCept, or are not sure when you took your last dose, take the regular amount of CellCept prescribed as soon as you remember. If it is time for your next dose, skip the missed dose. Do not take 2 doses at the same time. Call your healthcare provider if you are not sure what to do
- Take CellCept capsules, tablets and oral suspension on an empty stomach, either 1 hour before or 2 hours after a meal, unless your healthcare provider tells you otherwise. With the approval of your healthcare provider, in stable kidney transplant patients, CellCept can be taken with food if necessary
- Most people take CellCept by mouth either as blue and brown capsules or lavender tablets. Some people may get CellCept soon after their transplant surgery as an infusion into a vein
- Do not crush CellCept tablets. Do not open or crush CellCept capsules
- If you are not able to swallow CellCept tablets or capsules, your healthcare provider may prescribe CellCept Oral Suspension. This is a liquid form of CellCept. Your pharmacist will mix the medicine before giving it to you
- Do not mix CellCept Oral Suspension with any other medicine
- If you take too much CellCept, call your healthcare provider or the poison control center right away

What should I avoid while taking CellCept?

- Avoid pregnancy. See "What is the most important information I should know about CellCept?"
- Limit the amount of time you spend in sunlight. Avoid using tanning beds or sunlamps. People who take CellCept have a higher risk of getting skin cancer. (See "What is the most important information I should know about CellCept?") Wear protective clothing when you are in the sun and use a sunscreen with a high protection factor (SPF 30 and above). This is especially important if your skin is very fair or if you have a family history of skin cancer

What are the possible side effects of CellCept?

CellCept can cause serious side effects:

- See "What is the most important information I should know about CellCept?"
- Low blood cell counts. People taking high doses of CellCept each day may have a decrease in blood counts, including
  - white blood cells, especially neutrophils. Neutrophils fight against bacterial infections. You have a higher chance of getting an infection when your white blood cell count is low. This is most common from 3 months to 6 months after your transplant
  - red blood cells. Red blood cells carry oxygen to your body tissues. You have a higher chance of getting severe anemia when your red blood cell count is low
  - platelets. Platelets help with blood clotting
  Your healthcare provider will do blood tests before you start taking CellCept and during treatment with CellCept to check your blood cell counts.
  Tell your healthcare provider right away if you have any signs of infection (see "What is the most important information I should know about CellCept?"), or any unexpected bruising or bleeding. Also, tell your healthcare provider if you have unusual tiredness, lack of energy, dizziness or fainting.
- Stomach problems. Stomach and intestinal bleeding can happen in people who take high doses of CellCept. Bleeding can be severe and you may have to be hospitalized for treatment

Common side effects include:

- diarrhea. Call your healthcare provider right away if you have diarrhea. Do not stop taking CellCept without first talking with your healthcare provider
- vomiting
- pain
- stomach area pain
- swelling of the lower legs, ankles and feet
- high blood pressure

Side effects that happen more often in children than in adults taking CellCept include:

- stomach area pain
- fever
- infection
- pain
- blood infection (sepsis)
- diarrhea
- vomiting

- sore throat
- colds (respiratory tract infections)
- high blood pressure
- low white blood cell count
- low red blood cell count

These are not all of the possible side effects of CellCept. Tell your healthcare provider about any side effect that bothers you or that does not go away.

Call your doctor for medical advice about side effects. You may report side effects to the FDA at 1-800-FDA-1088 or to Genentech at 1-888-835-2555.

How should I store CellCept?

- Store CellCept capsules and tablets at room temperature, between 59°F to 86°F (15°C to 30°C). Keep the container closed tightly
- Store the prepared CellCept Oral Suspension at room temperature, between 59°F to 86°F (15°C to 30°C), for up to 60 days. You can also store CellCept Oral Suspension in the refrigerator at 36°F to 46°F (2°C to 8°C). Do not freeze CellCept Oral Suspension
- Keep CellCept and all medicines out of the reach of children

General Information about CellCept

Medicines are sometimes prescribed for purposes other than those listed in a Medication Guide. Do not use CellCept for a condition for which it was not prescribed. Do not give CellCept to other people, even if they have the same symptoms that you have. It may harm them.

This Medication Guide summarizes the most important information about CellCept. If you would like more information, talk with your doctor. You can ask your doctor or pharmacist for information about CellCept that is written for healthcare professionals. For more information, call 1-888-835-2555 or visit www.gene.com/gene/products/information/cellcept.

What are the ingredients in CellCept?

Active Ingredient: mycophenolate mofetil

Inactive Ingredients:

CellCept 250 mg capsules: croscarmellose sodium, magnesium stearate, povidone (K-90) and pregelatinized starch. The capsule shells contain black iron oxide, FD&C blue #2, gelatin, red iron oxide, silicon dioxide, sodium lauryl sulfate, titanium dioxide, and yellow iron oxide.

CellCept 500 mg tablets: black iron oxide, croscarmellose sodium, FD&C blue #2 aluminum lake, hydroxypropyl cellulose, hydroxypropyl methylcellulose, magnesium stearate, microcrystalline cellulose, polyethylene glycol 400, povidone (K-90), red iron oxide, talc, and titanium dioxide; may also contain ammonium hydroxide, ethyl alcohol, methyl alcohol, n-butyl alcohol, propylene glycol, and shellac.

CellCept Oral Suspension: aspartame, citric acid anhydrous, colloidal silicon dioxide, methylparaben, mixed fruit flavor, sodium citrate dihydrate, sorbitol, soybean lecithin, and xanthan gum.

CellCept Intravenous: polysorbate 80, and citric acid. Sodium hydroxide may have been used in the manufacture of CellCept Intravenous to adjust the pH.

This Medication Guide has been approved by the US Food and Drug Administration.

CELLCEPT, CYTOVENE-IV, and VALCYTE are registered trademarks of Hoffmann-La Roche Inc.
BACTRIM and BACTRIM DS are trademarks of Hoffmann-La Roche Inc.

Distributed by:
Genentech USA, Inc.
A Member of the Roche Group
1 DNA Way
South San Francisco, CA 94080-4990

Repackaged by:

Rebel Distributors Corp

Thousand Oaks, CA 91320

MG Revised: February 2010

For additional copies of this Medication Guide, please call 1-800-617-8191 or visit www.gene.com/gene/products/information/cellcept.

CTCTIO_1061443_PI/MG_AR2010_N(2)
CTCTIO_1061443_PI/MG_AR2010_K(2)

© 2010 Genentech, Inc. All rights reserved.

Representative sample of labeling (see the HOW SUPPLIED section for complete listing):

PRINCIPAL DISPLAY PANEL - 250 mg Capsule Carton

NDC 21695-171-00

CellCept®
(mycophenolate
mofetil capsules)

250 mg

Each capsule contains
250 mg mycophenolate mofetil.

Rx only

Attention Pharmacist: Dispense the
accompanying Medication Guide to each
patient. For additional Medication Guides
call 1-800-617-8191 or visit
www.gene.com/gene/
products/information/cellcept.

100 capsules

Rebel Distributors Corp